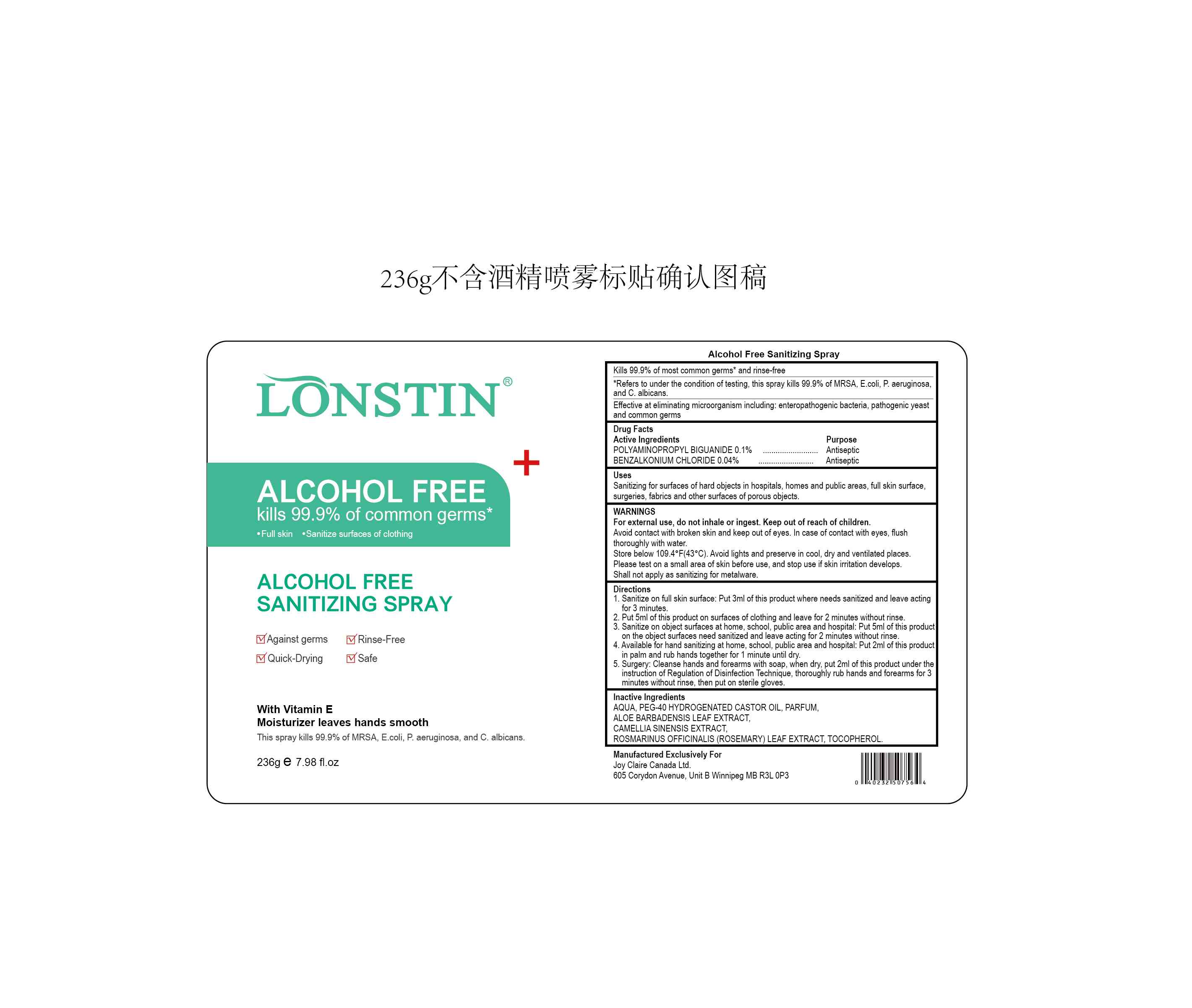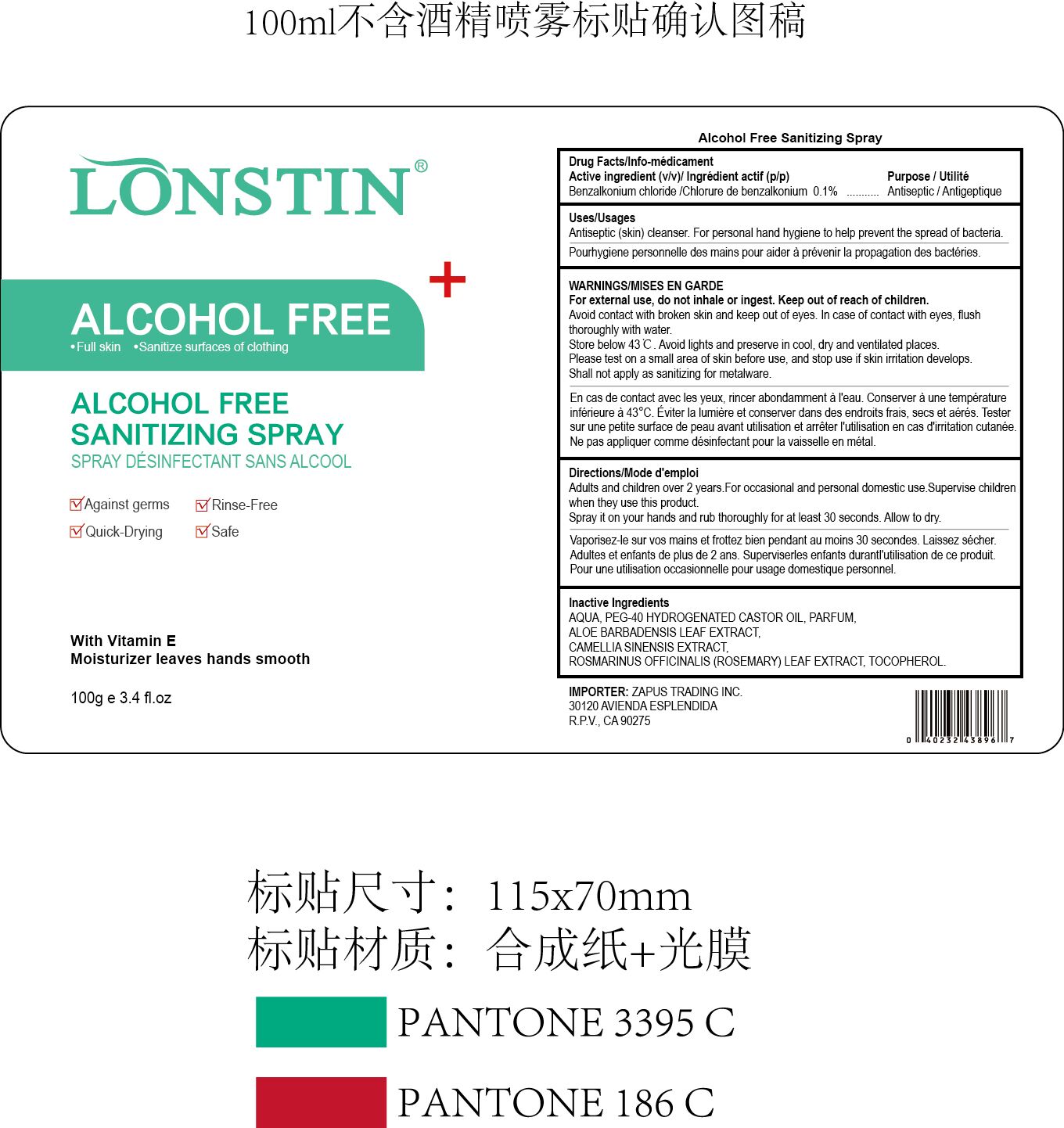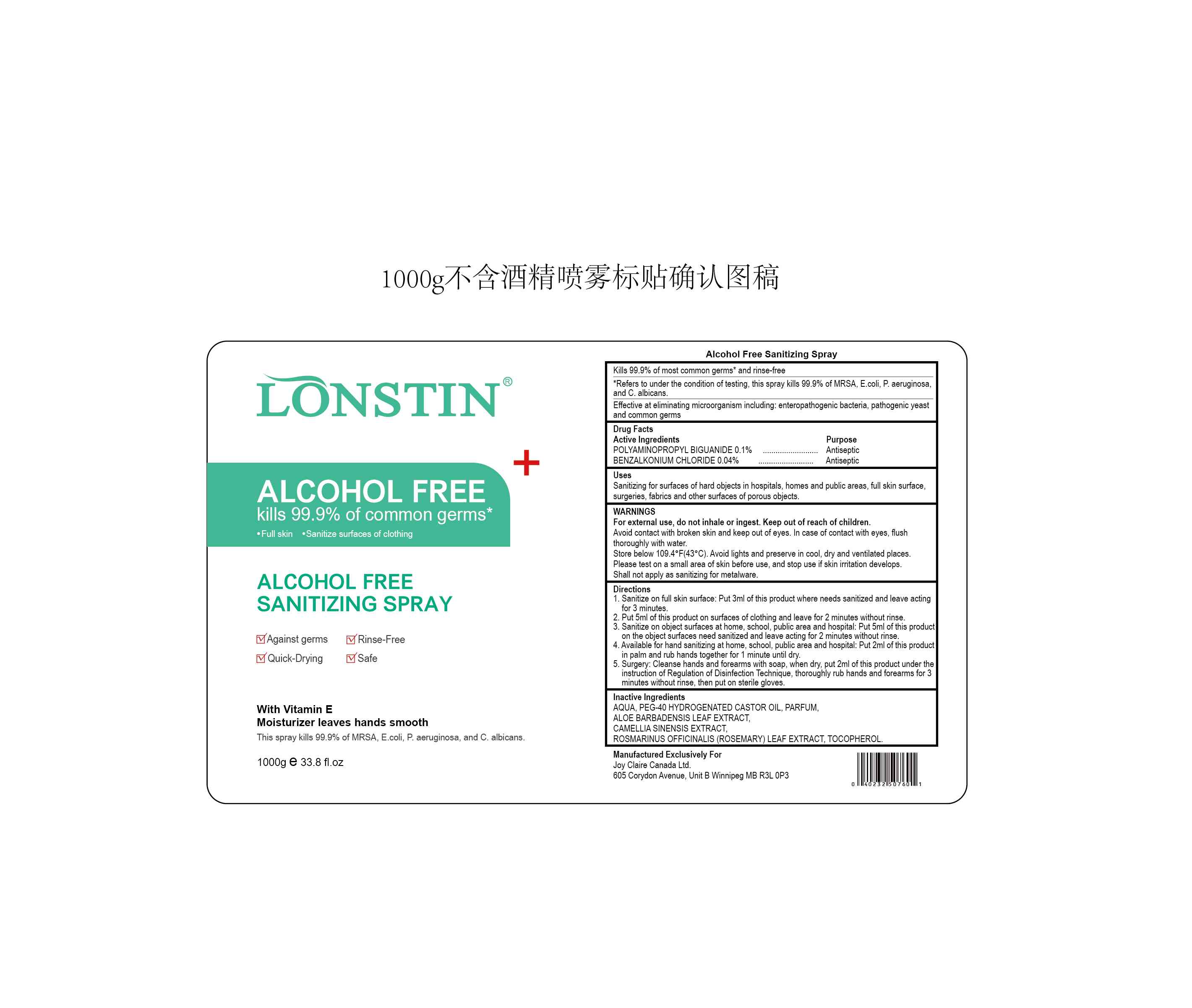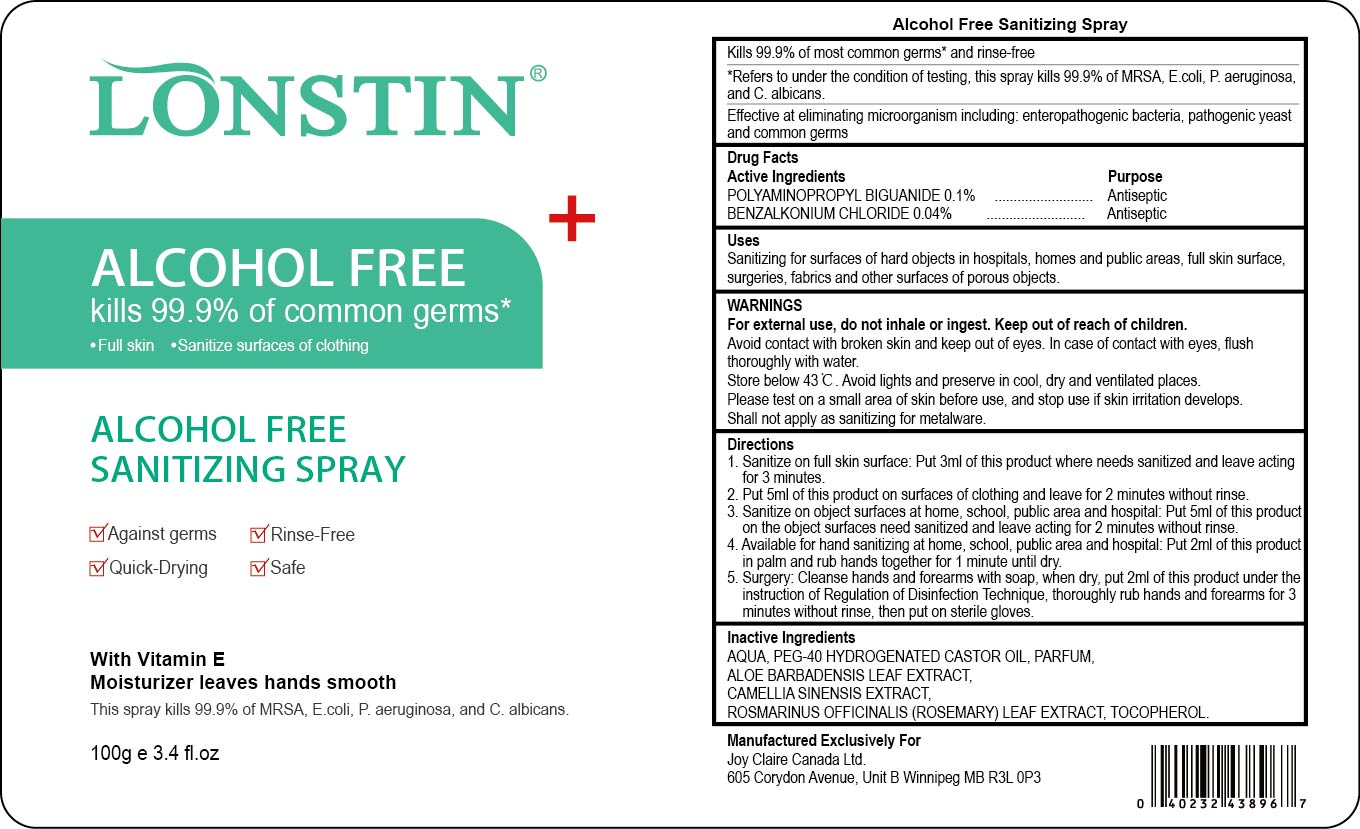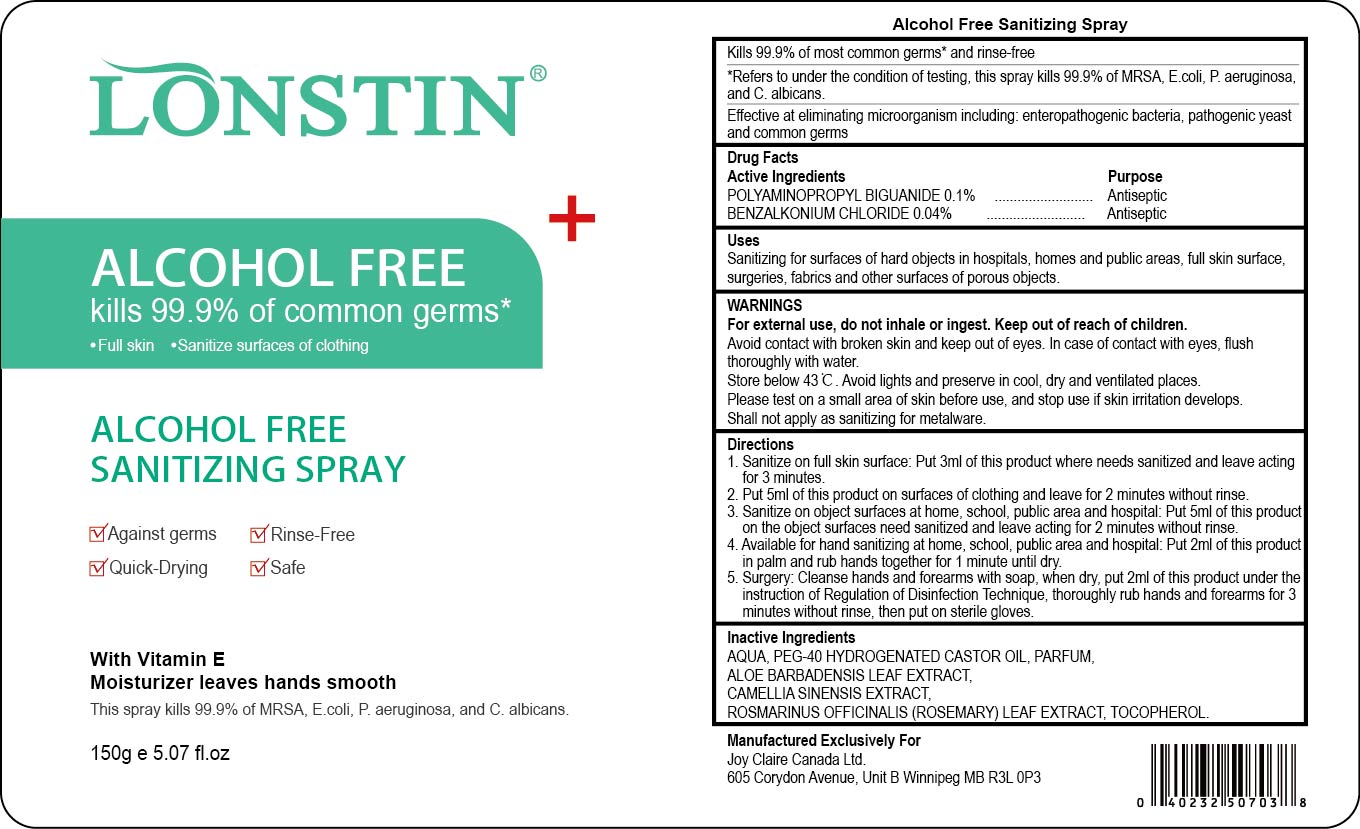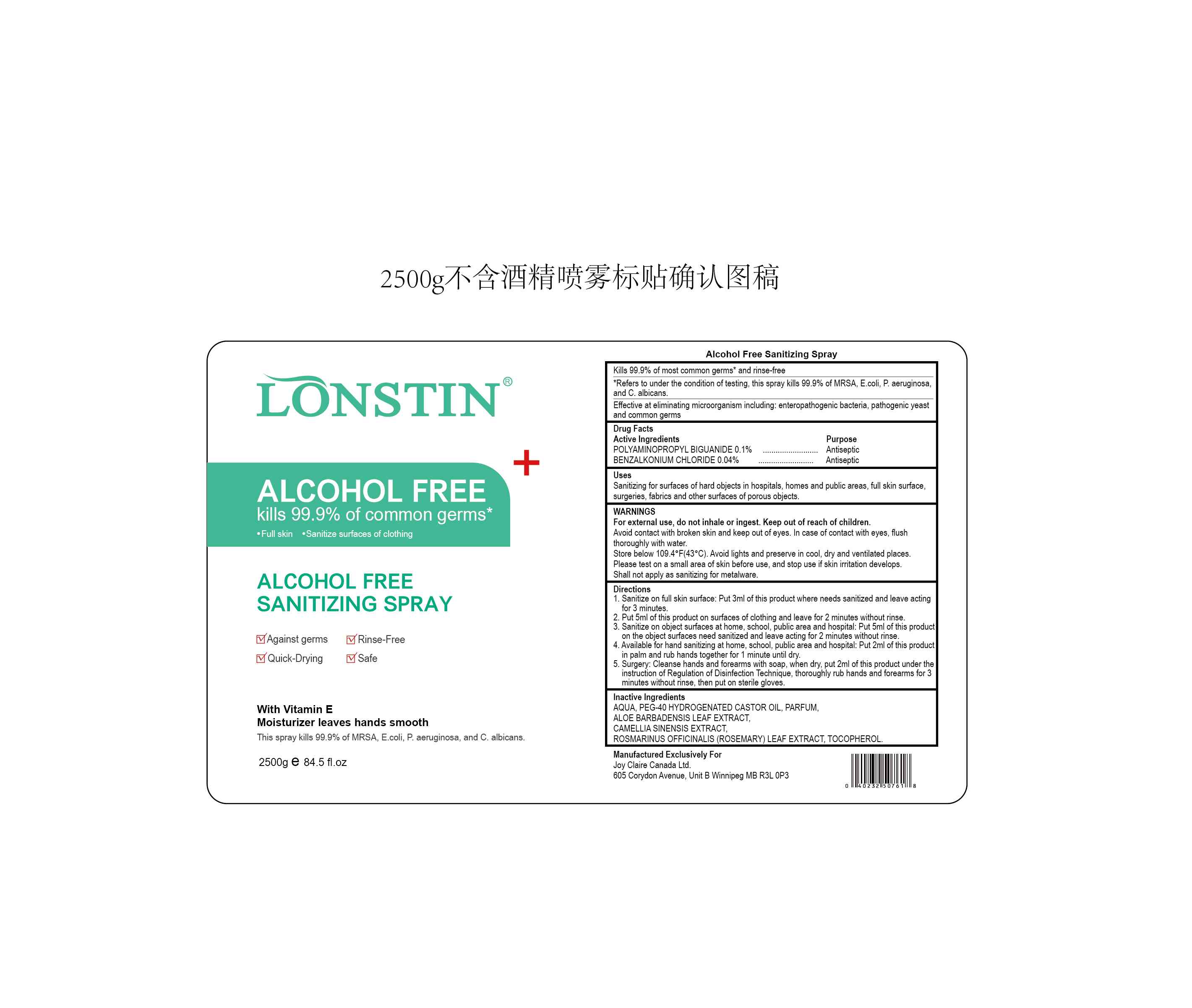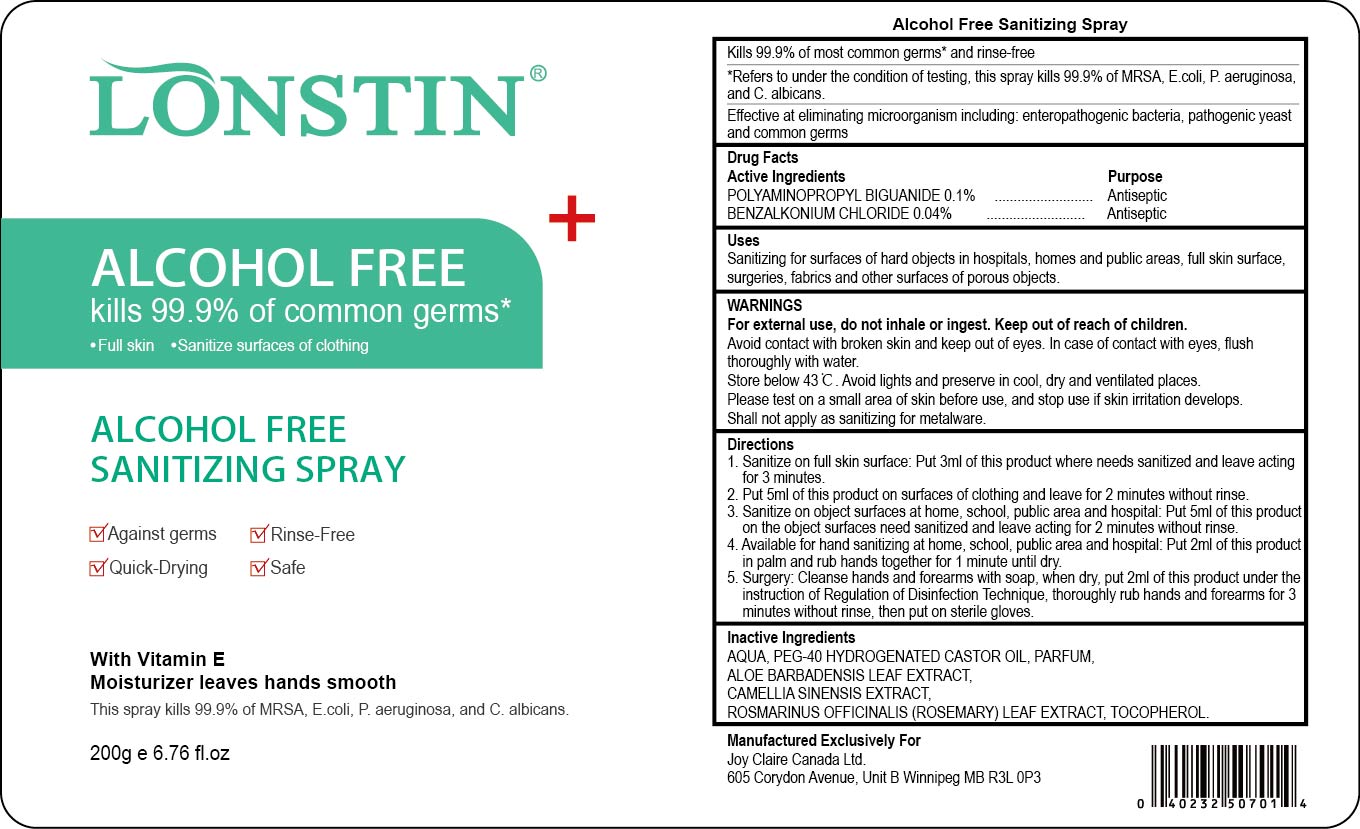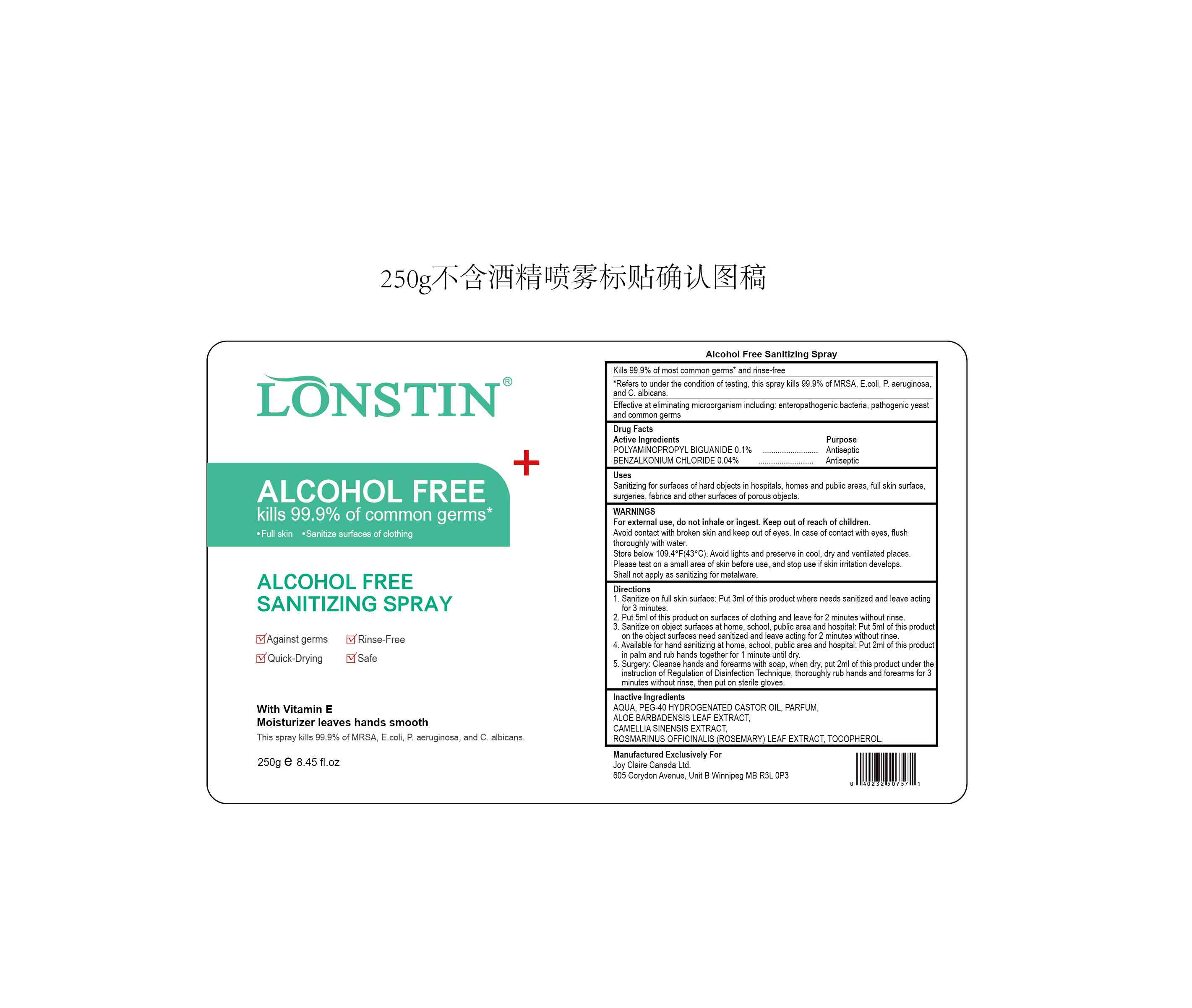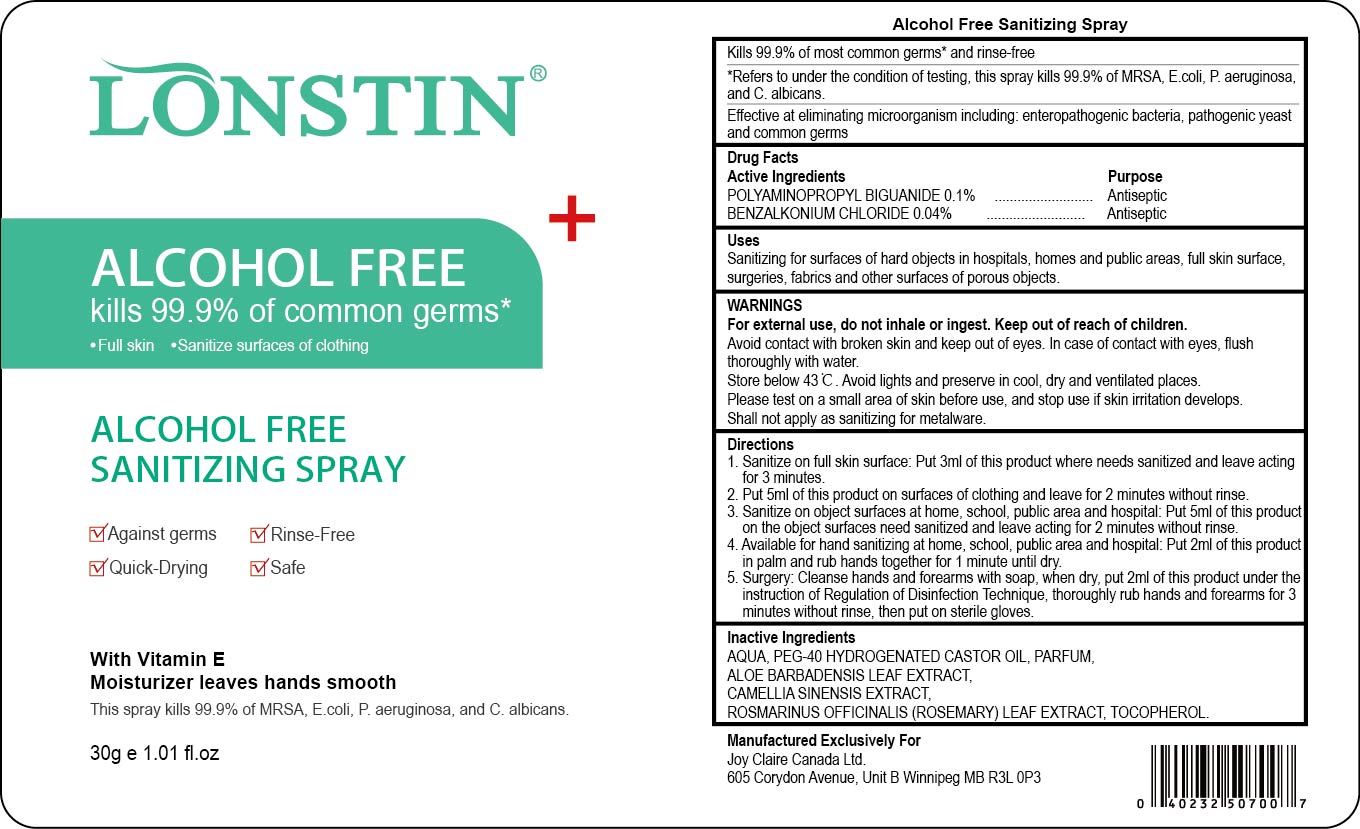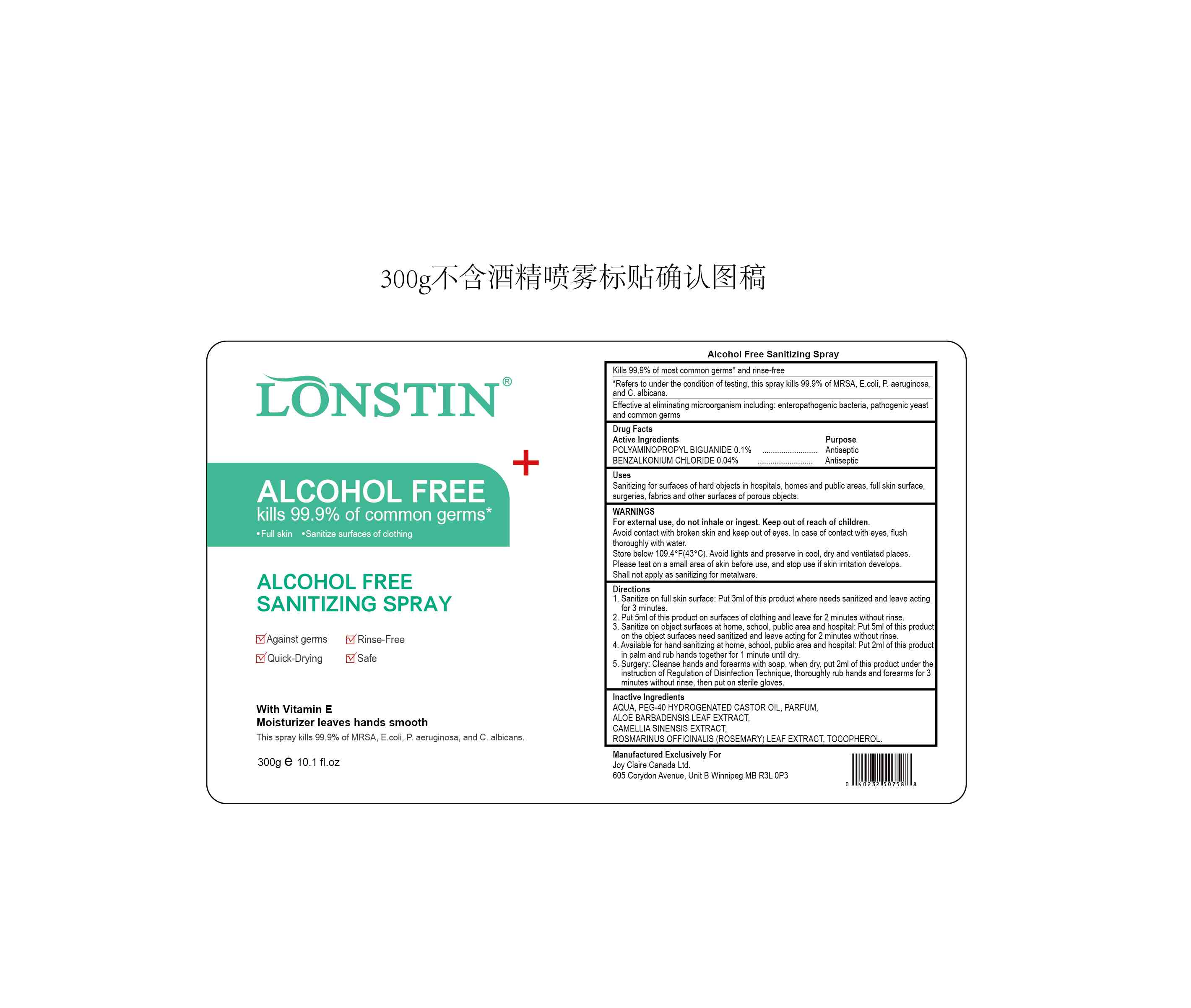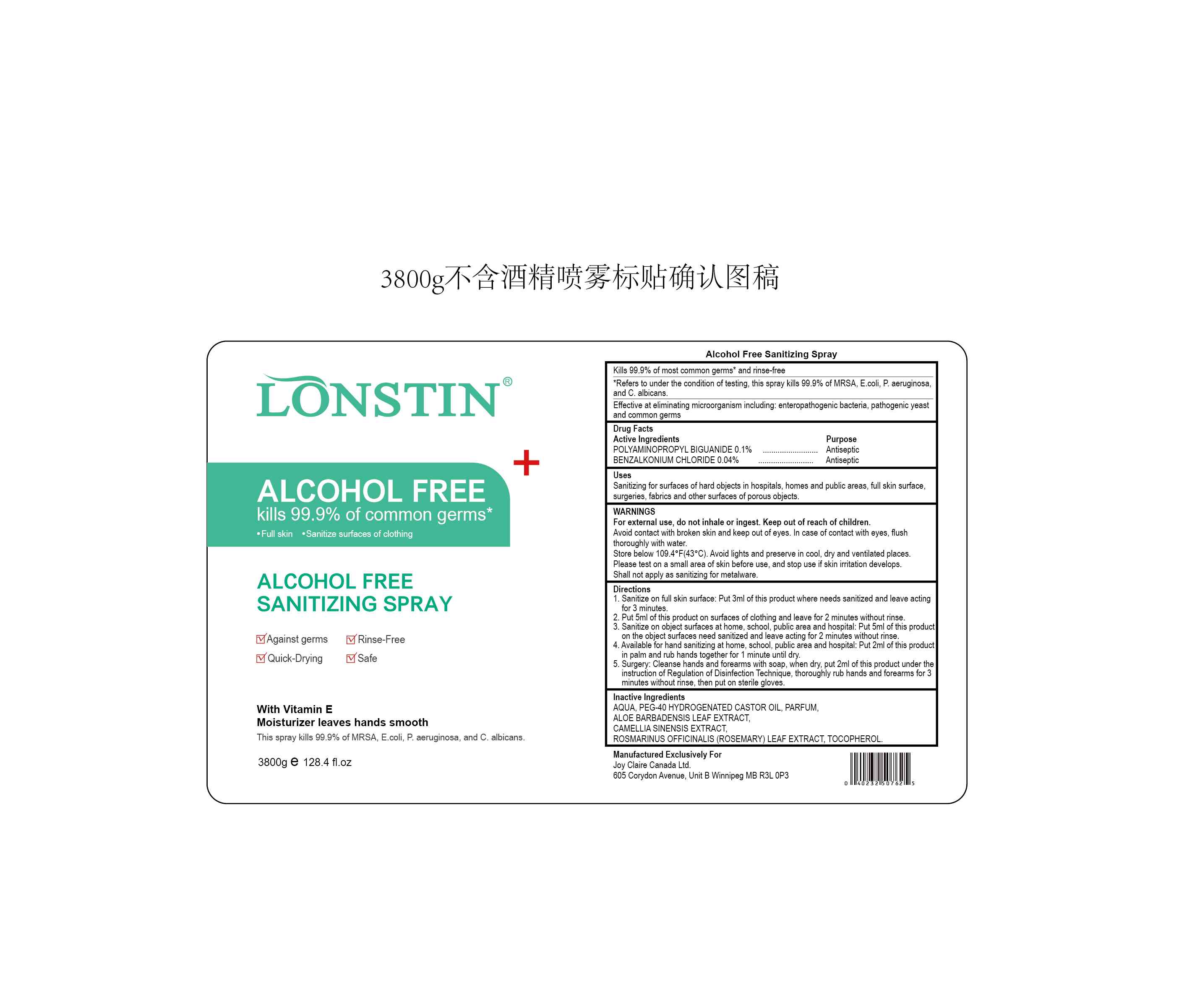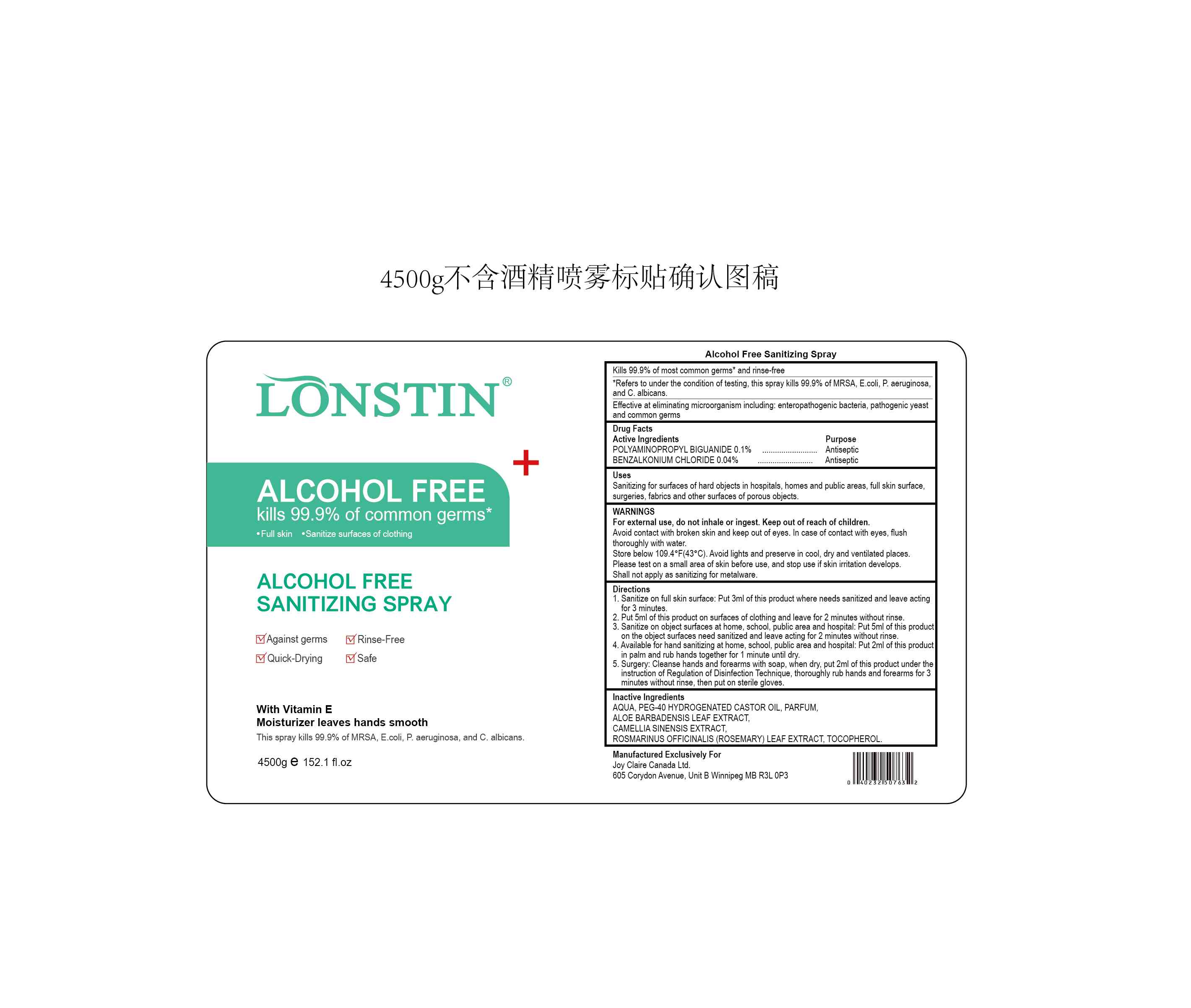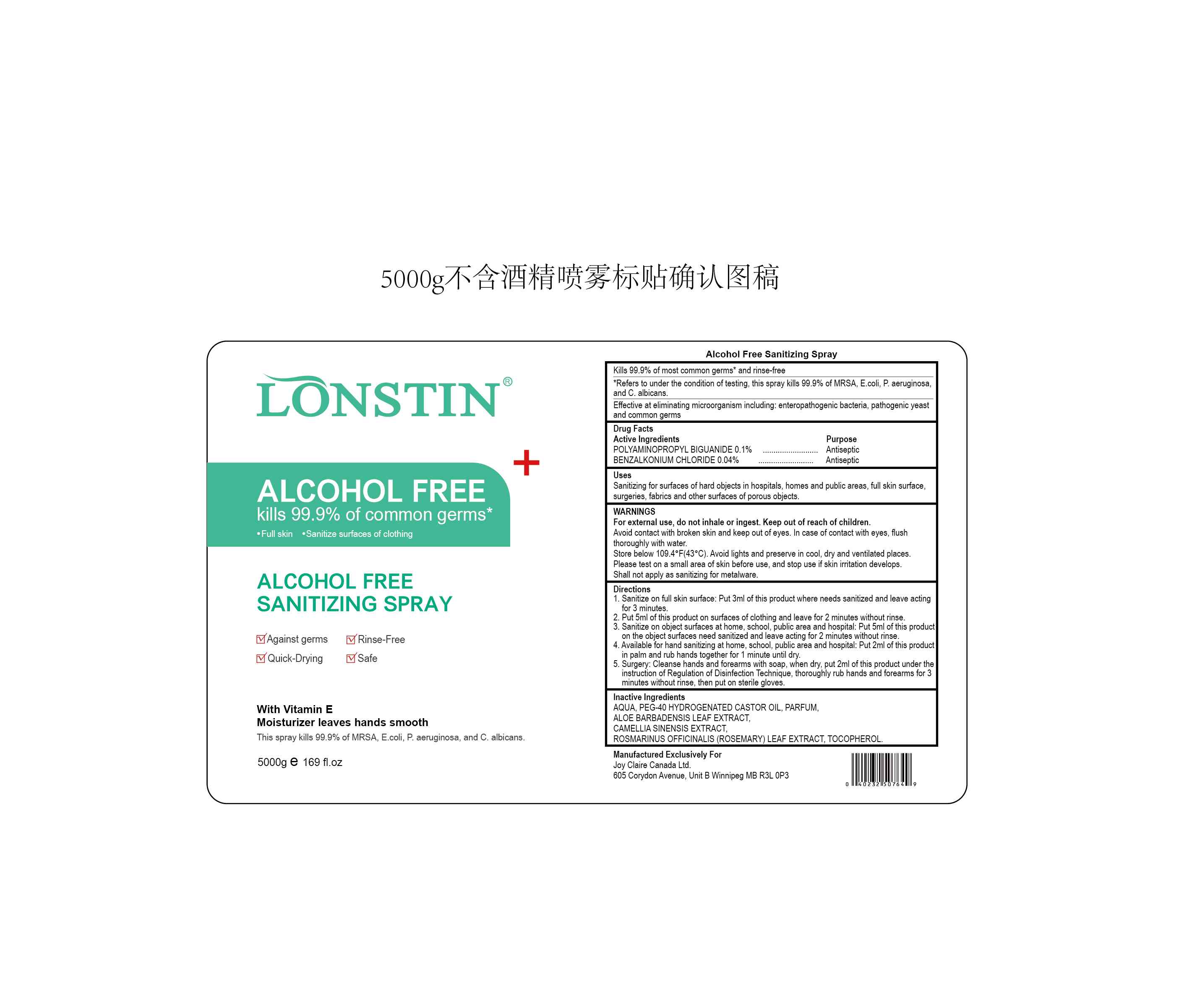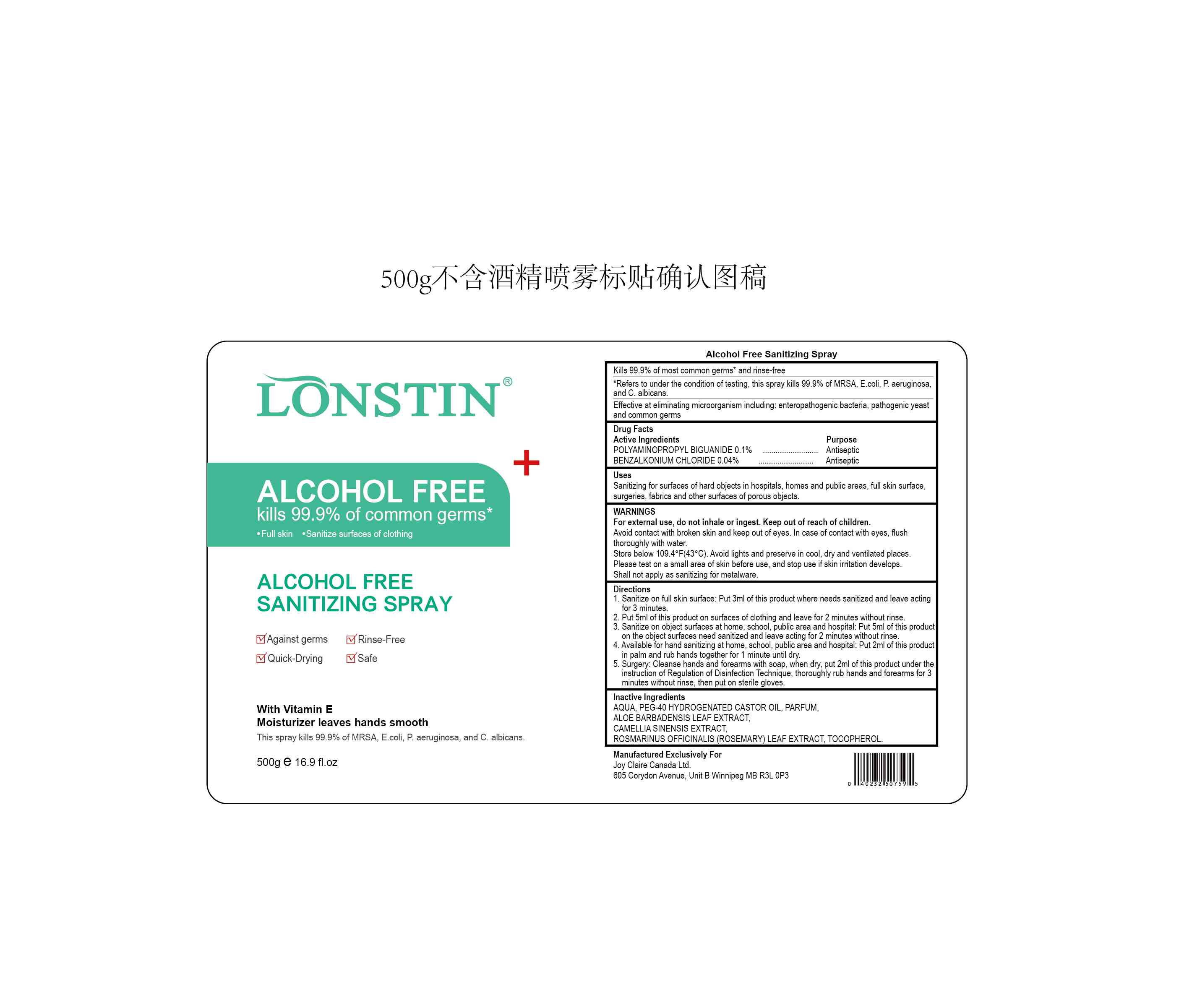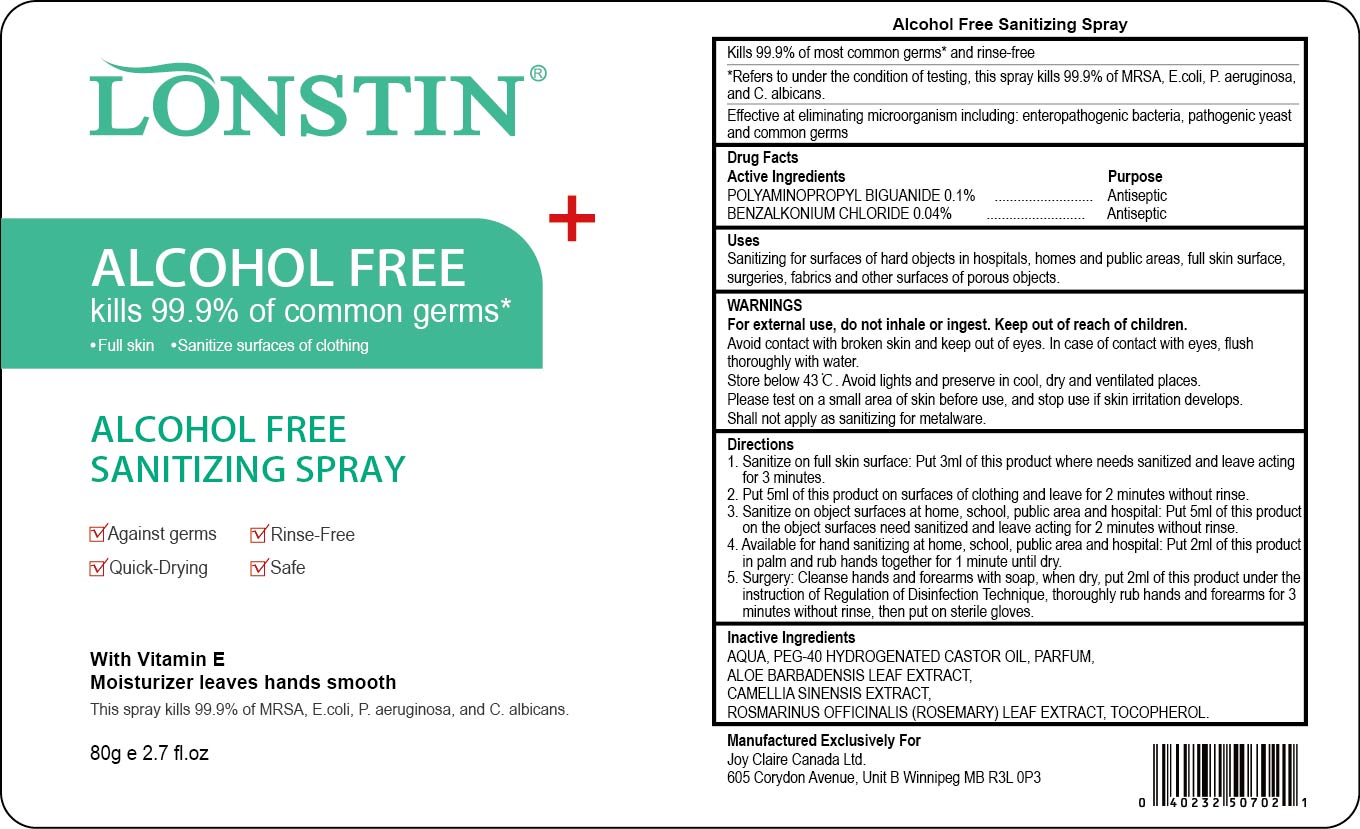 DRUG LABEL: ALCOHOL FREE SANITIZING
NDC: 74743-016 | Form: SPRAY
Manufacturer: Guangzhou Joy Claire Biological Technology   Co., Ltd
Category: otc | Type: HUMAN OTC DRUG LABEL
Date: 20200710

ACTIVE INGREDIENTS: BENZALKONIUM CHLORIDE 0.04 g/100 g; POLYAMINOPROPYL BIGUANIDE 0.1 g/100 g
INACTIVE INGREDIENTS: POLYOXYL 40 HYDROGENATED CASTOR OIL; WATER; ALOE; ROSEMARY; CAMELLIA SINENSIS SEED; ALPHA-TOCOPHEROL ACETATE; METHYL BENZOATE

ALCOHOL FREE SANITIZING SPRAY

SUMMARY OF SAFETY AND EFFECTIVENESS

- Kills 99. 9% of most common germs" and rinse-free
- Refers to under the condition of testing his spray kills 99. 9 %of MRSA E. ol, P aeruginosa and C albicans
- Effective at eliminating microorganism including enteropathogenic bacteria,pathogenic yeast and common germs

Active Ingredient(s)

POLYAMINOPROPYL BIGUANIDE 0. 1%

BENZALKONIUM CHLORIDE 0.04%

Purpose

Antiseptic

Use

Sanitizing for surfaces of hard objects in hospitals, homes and public areas, full skin surface,surgeres, fabrics and other surfaces of porous objects

Warnings

For external use, do not inhale or ingest.

Keep out of reach of children

Do not use

Avoid contact with broken skin and keep out of eyes.

WHEN USING

In case of contact with eyes, flush thoroughly with water

Other information

Store below 43 C Avoid lights and preserve in cool, dry and ventilated places

Directions

1. Sanitize on full skin surface Put 3 m of this product where needs sanitized and leave acting for 3 minutes
2. Put 5 m of this product on surfaces of clothing and leave for 2 minutes without rinse
3. Sanitize on object surfaces at home, school public area and hospital Put 5m of this product on the object surfaces need sanitized and leave acting for 2 minutes without rinse
4. Available for hand sanitizing at home, school public area and hospital. Put m of this product palm and rub hands together for 1 minute until dry
5. Surgery: Cleanse hands and forearms with soap when dry, put 2 m of this product under the instruction of Regulation of Deon Technique thoroughly rub hands and forearms for 3 minutes without rinse, then put on sterile gloves

Directions

- Place enough product on hands to cover all surfaces. Rub hands together until dry.
- Supervise children under 6 years of age when using this product to avoid swallowing.

Inactive ingredients

AQUA ,PEG-40 HYDROGENATED CASTOR OIL, PARFUM,
ALOE BARBADENSIS LEAF EXTRACT,
CAMELLIA SINENSIS EXTRACT,
ROSMARINUS OFFICINALIS(ROSEMARY) LEAF EXTRACT, TOCOPHEROL